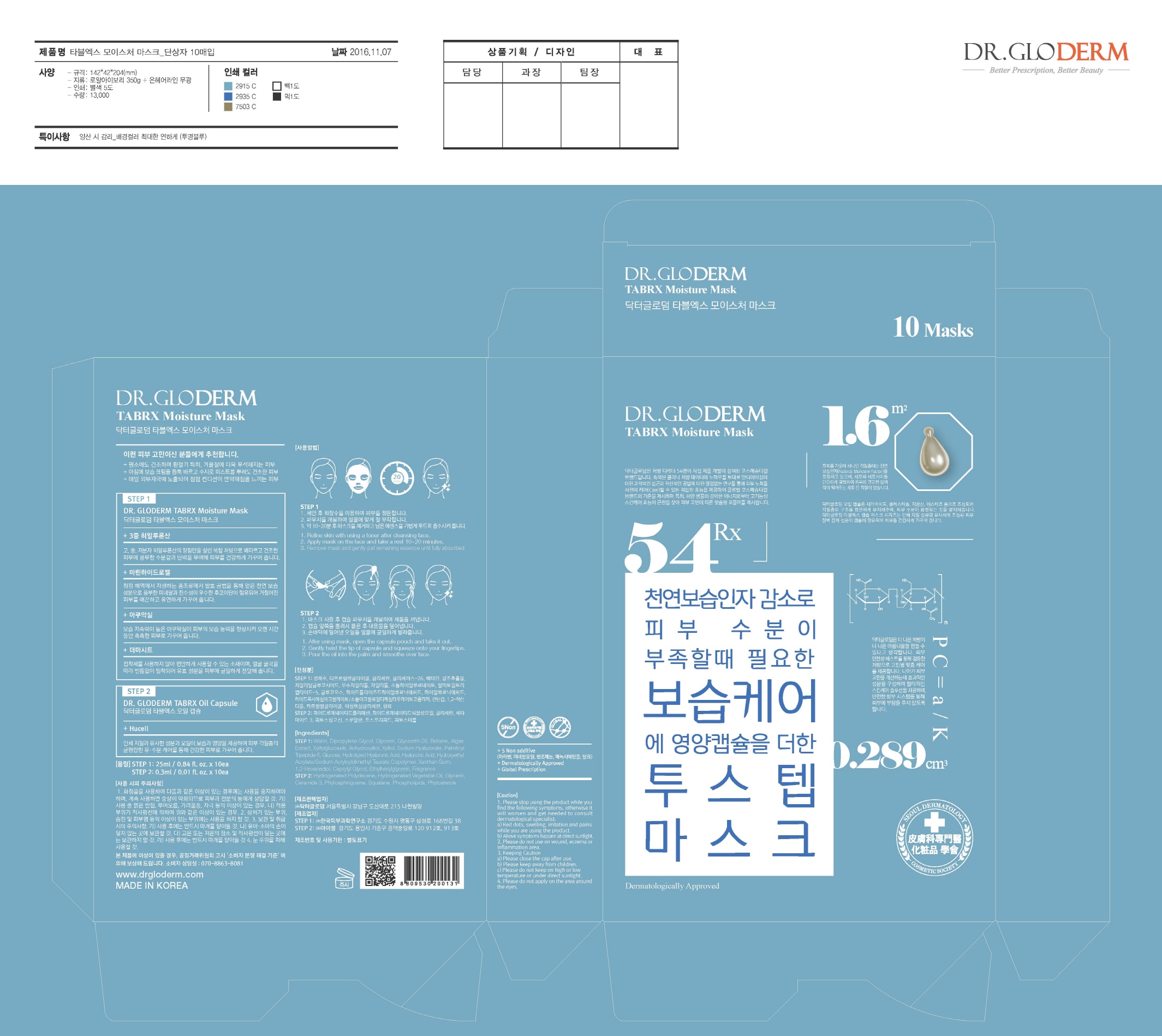 DRUG LABEL: DR. GLODERM TABRX MOISTURE MASK
NDC: 71342-0005 | Form: KIT | Route: TOPICAL
Manufacturer: DR.GLODERM
Category: otc | Type: HUMAN OTC DRUG LABEL
Date: 20170331

ACTIVE INGREDIENTS: GLYCERIN 5 g/100 mL; GLYCERIN 1 g/100 mL
INACTIVE INGREDIENTS: WATER; HYALURONATE SODIUM; SQUALANE

ACTIVE INGREDIENT

Step1(Mask): Glycerin
Step2(Oil Capsule): Glycerin

INACTIVE INGREDIENT

Step1: Water, Sodium Hyaluronate, etc
Step2: Hydrogenated Polydecene, Hydrogenated Vegetable Oil, etc

PURPOSE

Skin Protectant - Moisture

WARNINGS

1. If the following symptoms occur after product use, stop using the product immediately and consult a dermatologist (continuous use can exacerbate the symptoms).
1) Occurrence of red spots, swelling, itchiness, and other skin irritation
2) If the symptoms above occur after the application area is exposed to direct sunlight

2. Do not use on open wounds, eczema, and other skin irritations
3. Precaution for Storage and Handling
1) Close the lid after use
2) Keep out of reach of infants and children
3) Do not to store in a place with high/low temperature and exposed to direct sunlight

4. Use as avoiding eye areas.

Keep out of reach of children.

INDICATIONS AND USAGE

Step1

1. Refine skin with using a toner after cleansing face.
2. Apply mask on the face and take a rest 10~20 minutes.
3. Remove mask and gently pat remaining essence until fully absorbed.

Step2

1. After using mask, open the capsule pouch and take it out.
2. Gently twist the tip of capsule and squeeze onto your fingertips.
3. Pour the oil into the palm and smoothe over face.

DOSAGE AND ADMINISTRATION

for external use only